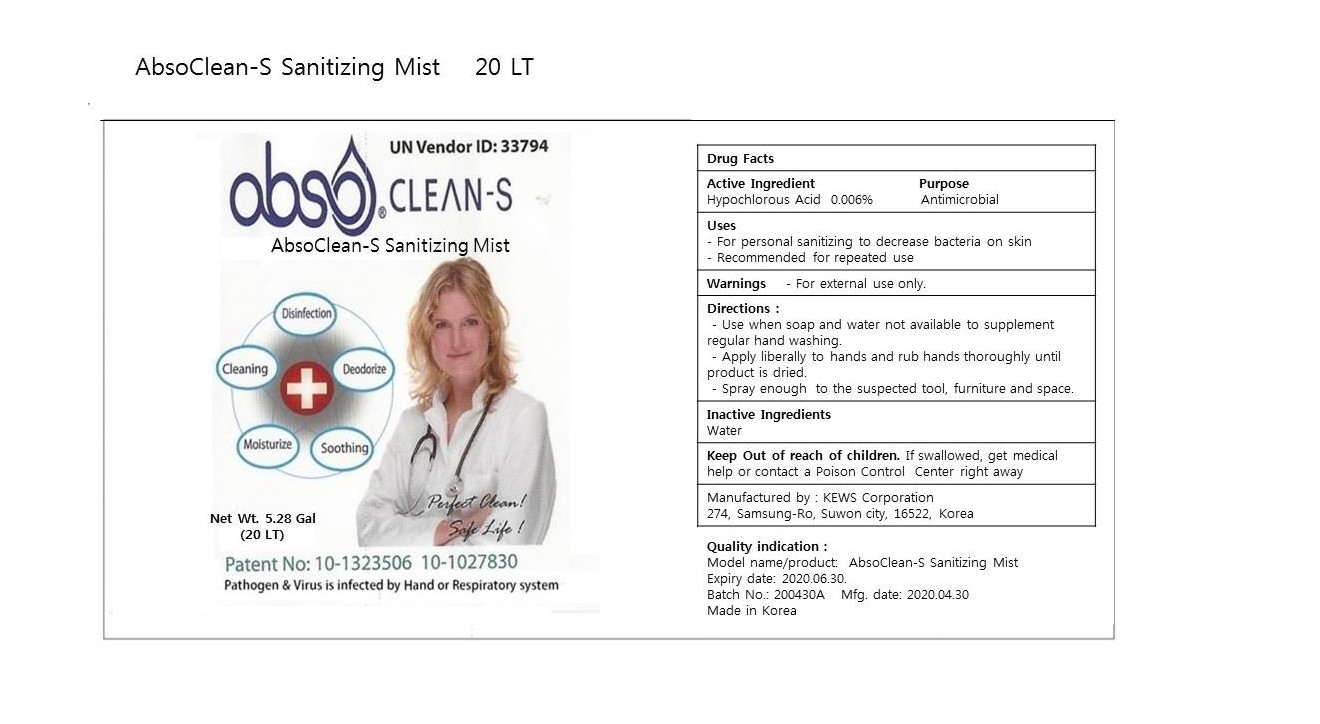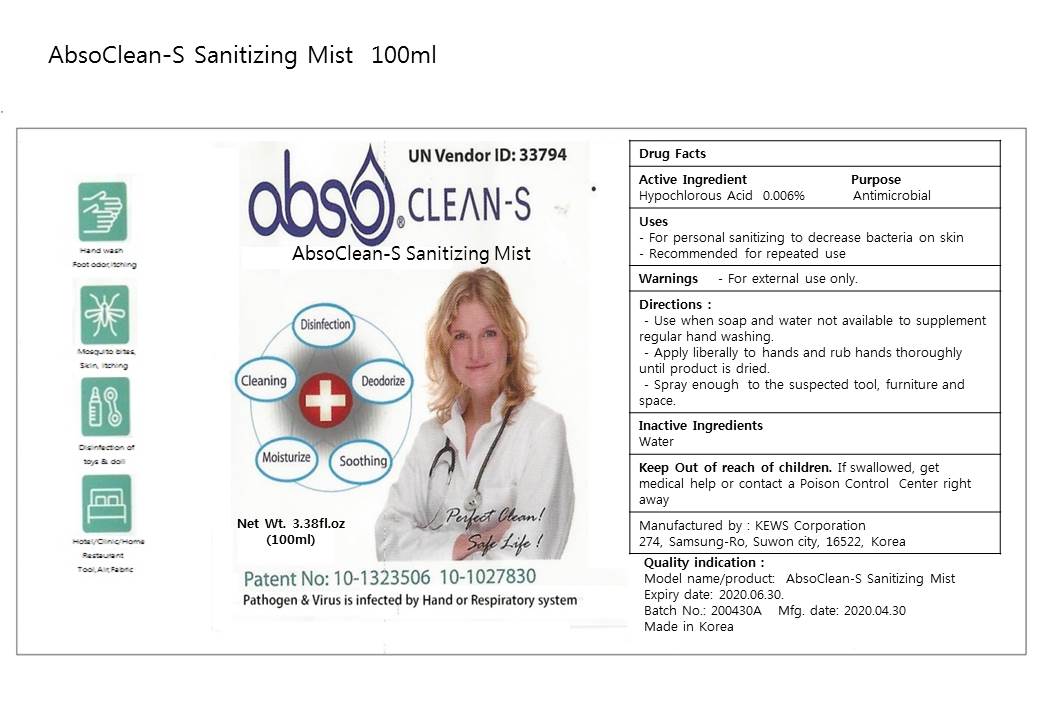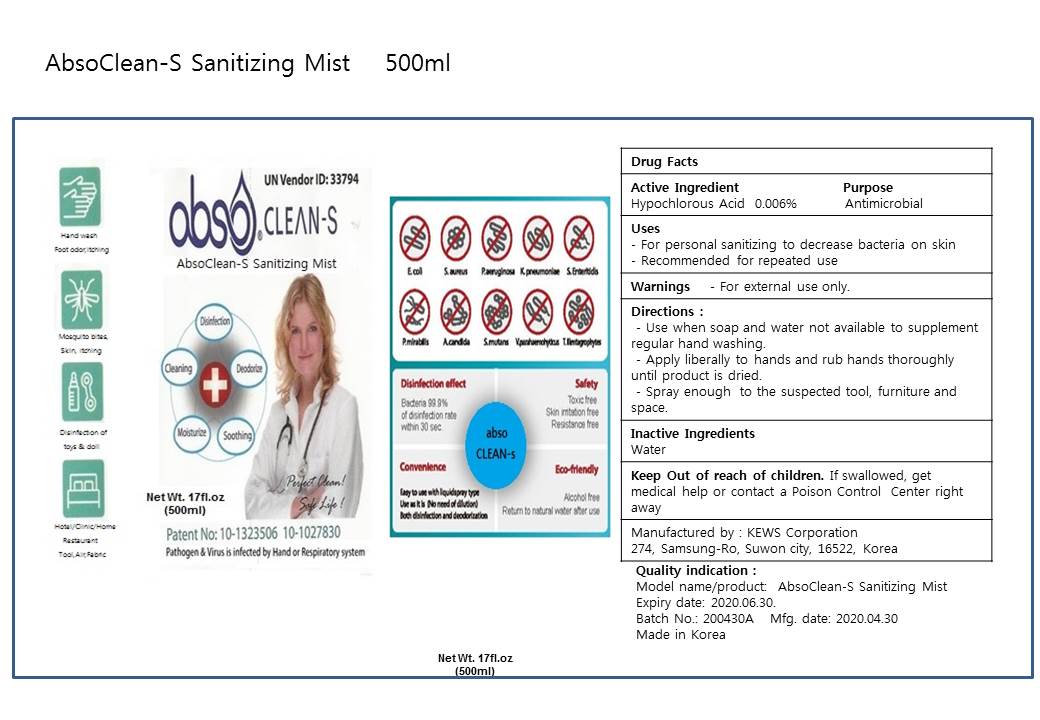 DRUG LABEL: AbsoClean-S Sanitizing Mist
NDC: 75644-002 | Form: LIQUID
Manufacturer: KEWS CORPORATION
Category: otc | Type: HUMAN OTC DRUG LABEL
Date: 20220118

ACTIVE INGREDIENTS: HYPOCHLOROUS ACID 0.006 mg/1 mL
INACTIVE INGREDIENTS: WATER

AbsoClean-S Sanitizing Mist

ACTIVE INGREDIENT

HYPOCHLOROUS ACID -- 0.006%

Inactive Ingredients

Water

Purpose

Antimicrobial

Directions for Use

-Use when soap and water not available to supplement regular hand washing.

-Apply liberally to hands and rub hands thorougly until product is dried

-Spray enough to the suspected tool, furniture and space.

Intended Use

-For personal sanitizing to decrease bacteria on skin

-Recommended for repeated use

Purpose

-For personal sanitzing to decrease bacteria on skin

-Recommended for repeated use

Warnings

For External Use

Keep out of reach of children.

If swallowed, get medical help or contact a Poison Control Center right away.

100mL PDP

100mL NDC 75644-002-01

500mL PDP

500mL NDC 75644-002-02

20LT PDP

20LT NDC 75644-002-03